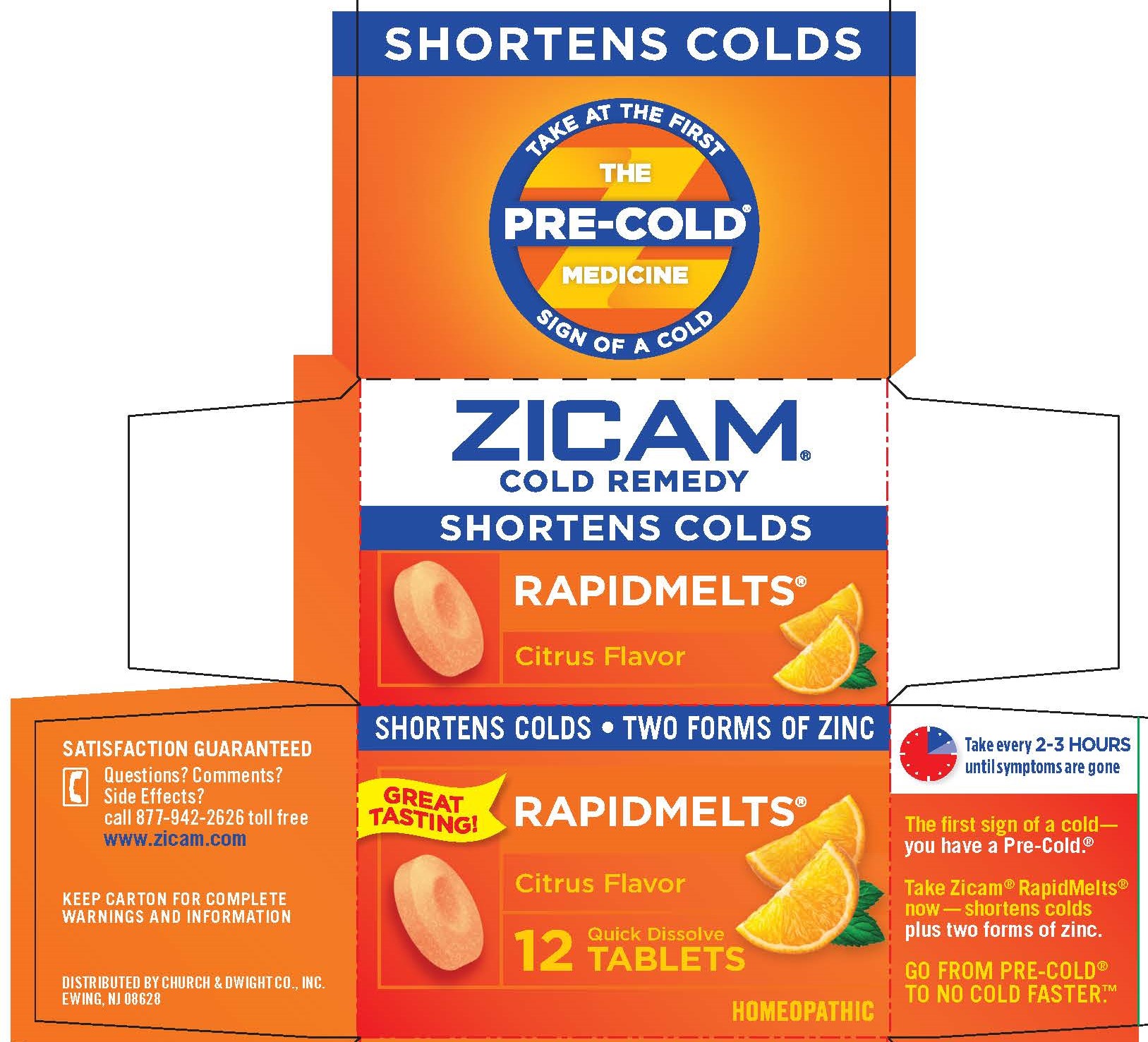 DRUG LABEL: Zicam
NDC: 10237-460 | Form: TABLET
Manufacturer: Church & Dwight Co., Inc.
Category: homeopathic | Type: HUMAN OTC DRUG LABEL
Date: 20251204

ACTIVE INGREDIENTS: ZINC ACETATE ANHYDROUS 2 [hp_X]/1 1; ZINC GLUCONATE 1 [hp_X]/1 1
INACTIVE INGREDIENTS: ASCORBIC ACID; CROSPOVIDONE (120 .MU.M); FD&C YELLOW NO. 6; ALUMINUM OXIDE; MAGNESIUM STEARATE; MANNITOL; AMMONIUM GLYCYRRHIZATE; STEARIC ACID; SUCRALOSE; SODIUM STARCH GLYCOLATE TYPE A POTATO

Zicam®Cold Remedy Rapidmelts®Citrus

Active ingredients (in each tablet)

Zincum aceticum 2x
Zincum gluconicum 1x

Purpose

Reduces duration of the common cold and helps relieve nasal congestion

Uses

Reduces duration of the common cold and helps relieve nasal congestion.

Zicam®Cold Remedy was not formulated to be effective for flu or allergies.

Warnings

ASK DOCTOR

If you are allergic or sensitive to zinc, consult a doctor before using

Stop use and ask a doctor ifsymptoms persist or are accompanied by a fever or new symptoms occur

PREGNANCY OR BREAST FEEDING

If pregnant or breast-feeding,ask a health professional before use.

Keep out of reach of children.In case of overdose, get medical help or contact a Poison Control Center right away.

Directions

- for best results, use at the first sign of a cold and continue to use until symptoms completely subside
- adults and children 12 years of age and older:
  - take 1 tablet at the onset of symptoms
  - dissolve entire tablet in mouth. Do not chew. Do not swallow whole.
  - repeat every 2–3 hours, not to exceed 7 tablets in 24 hours. Take until symptoms are gone.
  - to avoid minor stomach upset, do not take on an empty stomach
  - do not eat or drink for 15 minutes after use. Do not eat or drink citrus fruits or juices for 30 minutes before or after use. Otherwise, drink plenty of fluids.
- children under 12 years of age: ask a doctor before use

Other information

- store between 15-29°C (59-84°F)

Inactive ingredients

ascorbic acid, crospovidone, FD&C yellow no. 6 aluminum lake, magnesium stearate, mannitol, mono-ammonium glycyrrhizinate, natural and artificial flavor, sodium starch glycolate, stearic acid, sucralose

Questions? Comments? Side Effects?

call 877-942-2626 toll free

www.zicam.com

PRINCIPAL DISPLAY PANEL - 25 Tablet Bottle Carton

SHORTEN COLDS

TAKE AT THE FIRST SIGN OF A COLD

THE PRE-COLD MEDICINE

ZICAM

COLD REMEDY

SHORTENS COLDS

RAPIDMELTS®

Citrus Flavor

SHORTENS COLDS • TWO FORMS OF ZINC

GREAT TASTING!

RAPIDMELTS®

Citrus Flavor

12 Quick Dissolve TABLETS

HOMEOPATHIC